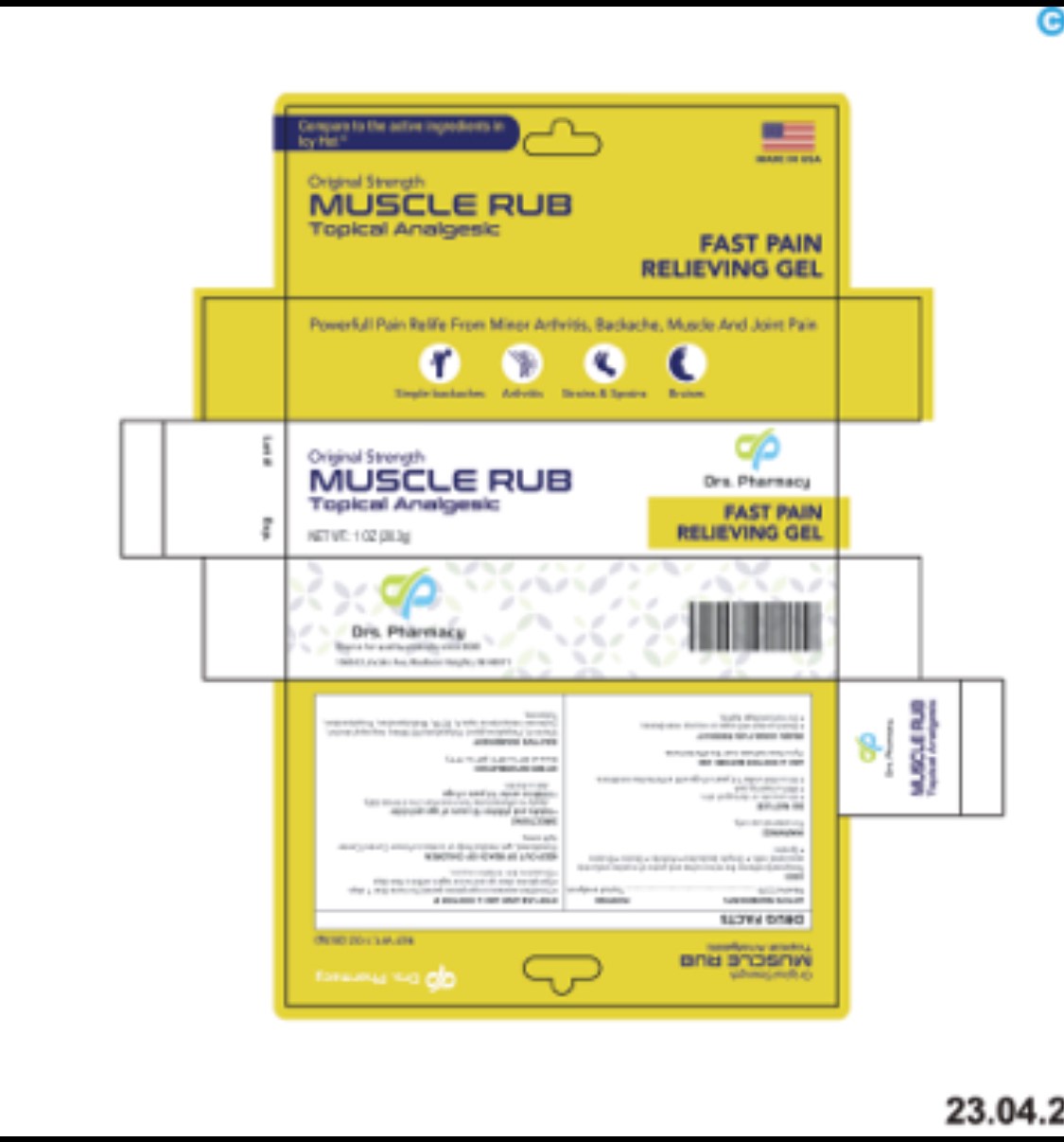 DRUG LABEL: MUSCLE RUB
NDC: 80489-004 | Form: GEL
Manufacturer: OL PHARMA TECH,LLC
Category: otc | Type: HUMAN OTC DRUG LABEL
Date: 20250109

ACTIVE INGREDIENTS: MENTHOL, UNSPECIFIED FORM 25 mg/1 g
INACTIVE INGREDIENTS: ISOPROPYL ALCOHOL; WATER; CARBOMER INTERPOLYMER TYPE A (55000 CPS); PROPYLENE GLYCOL; EDETATE DISODIUM; .ALPHA.-TOCOPHEROL; TROLAMINE; POLYSORBATE 80; METHYLPARABEN

ACTIVE INGREDIENT

MENTHOL 2.5%

PURPOSE

TOPICAL ANALGESIC

USES

temporarily relieves the minor aches and pains of muscles and joints associated with:

- simple backaches
- arthritis
- strains
- bruises
- sprains

WARNINGS

For external use only

Do not use

- on wounds or damaged skin
- with a heating pad
- on a child under 12 years of age with arthritis-like conditions

When using this product

- avoid contact with eyes or mucous membranes
- do not bandage tightly

Stop use and ask your doctor if:

- condition worsens or symptoms persist for more than 7 days
- symptoms clear up and occur again within a few days
- excessive skin irritation occurs

Keep out of reach of children. If swallowed, get medical help or contact a Poison Control Center immediately.

Directions

- adults and children 12 years of age and older: apply to affected area not more than 3 to 4 times daily
- children under 12 years of age: ask a doctor

Other Information

store at 20° to 25°C (68° to 77°F)

Inactive Ingredients

vitamin E, propylene glycol, polysorbate 80, water, isopropyl alcohol, carbomer interpolymer type A, EDTA , methylparaben, propylparaben

Questions

www.drspharmacyusa.com

PACKAGE LABEL

- original strenghth
- Topical analgesic